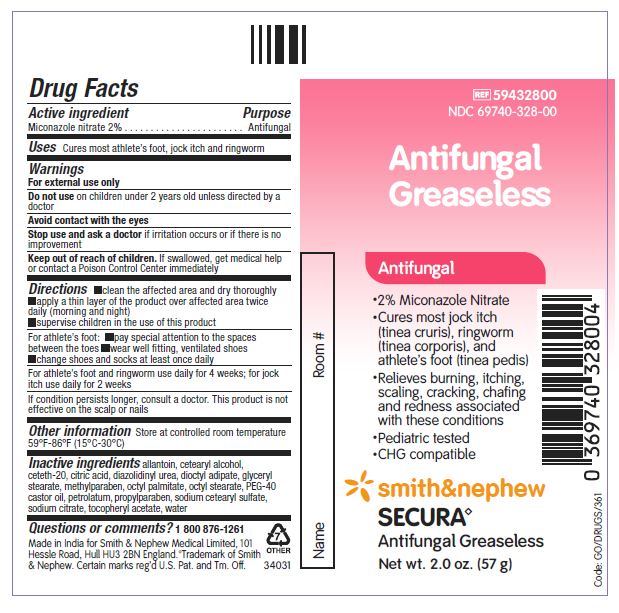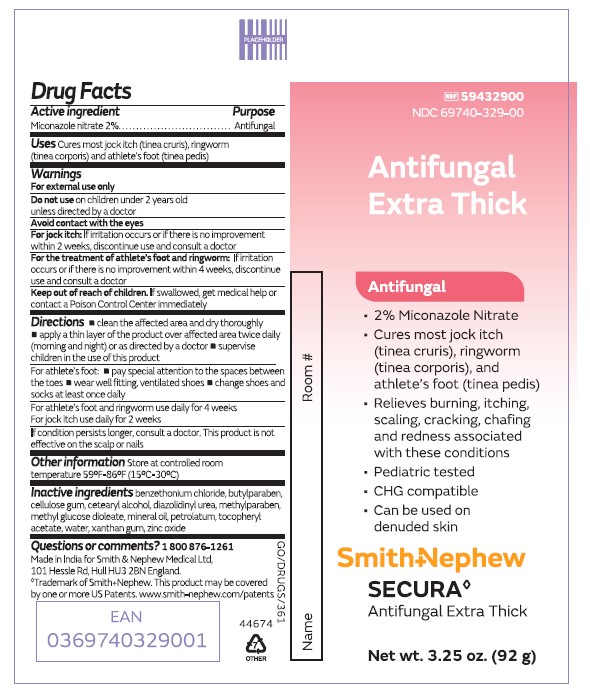 DRUG LABEL: Secura Antifungal
NDC: 69740-328 | Form: CREAM
Manufacturer: Smith & Nephew Medical Ltd
Category: otc | Type: HUMAN OTC DRUG LABEL
Date: 20250417

ACTIVE INGREDIENTS: MICONAZOLE NITRATE 20 mg/1 g
INACTIVE INGREDIENTS: DIHEPTYL ADIPATE; PEG-40 CASTOR OIL; PROPYLPARABEN; OCTYL PALMITATE; ANHYDROUS CITRIC ACID; OCTYL STEARATE; ALLANTOIN; DIAZOLIDINYL UREA; GLYCERYL MONOSTEARATE; METHYLPARABEN; ALPHA-TOCOPHEROL ACETATE; PETROLATUM; SODIUM CETOSTEARYL SULFATE; SODIUM CITRATE; WATER; CETOSTEARYL ALCOHOL; CETETH-20

Secura Antifungal

ACTIVE INGREDIENTS

Miconazole nitrate 2%

PURPOSE

Antifungal

USES

Antifungal Extra Thick

Cures most jock itch (tinea cruris), ringworm (tinea corporis) and athlete's foot (tinea pedis)

Antifungal Greaseless

Cures most athlete's foot, jock itch and ringworm

WARNINGS

- For external use only
- Do not use on children under 2 years old unless directed by a doctor

- Avoid contact with the eyes
- For jock itch: If irritation occurs or it there is no improvement within 2 weeks, discontinue use and consult a doctor
- For the treatment of athlete's foot and ringworm: If irritaion occurs or it there is no improvement within 4 weeks, discontinue use and consult a doctor
- Keep out of reach of children. If swallowed, get medical help or contact a Poison Control Center immediately

Updated in line with latest OTC Monograph

Addition of 'Unless directed by doctor' to 'Do not use on children under 2 years old'.
Separation and expansion of 'For jock itch' and 'For athlete's foot and ringworm' warnings

KEEP OUT OF REACH OF CHILDREN

- Keep reach out of children. If swallowed, get medical help or contact a Poison Control Center immediately

DIRECTIONS

- clean the affected area and dry thoroughly
- apply a thin layer of the product over affected area twice daily (morning and night) or as directed by a doctor
- supervise children in the use of this product

For athlete's foot:

- pay special attention to the spaces between the toes
- wear well fitting, ventilated shoes
- change shoes and socks at least once daily

For athlete's foot and ringworm use daily for 4 weeks.

For jock itch use daily for 2 weeks.

If condition persists longer, consult a doctor. This product is not effective on the scalp or nails.

QUESTION OR COMMENTS?

1 800 876-1261

INACTIVE INGREDIENTS

Antifungal Greaseless
allantoin, cetearyl alcohol, ceteth-20, citric acid, diazolidinyl urea, dioctyl adipate, glyceryl stearate, methylparaben, octyl palmitate, octyl stearate, PEG-40 castor oil, petrolatum, propylparaben, sodium cetearyl sulfate, sodium citrate, tocopheryl acetate, water

Antifungal Extra Thick
benzethonium chloride, butylparaben, cellulose gum, diazolidinyl urea, methylparaben, methyl glucose dioleate, mineral oil, petrolatum, tocopheryl acetate, water, xanthan gum, zinc oxide

PACKAGE LABEL

PACKAGE LABEL - PRINCIPAL DISPLAY PANEL - SECURA ANTIFUNGAL EXTRA THICK - TUBE(92g)

Item #59432900

NDC 69740-329-00

Antifungal Extra Thick

2% Miconazole Nitrate
Cures most jock itch (tinea cruris), ringworm (tinea corporis), and athlete's foot (tinea pedis)
Relieves burning, itching, scaling, cracking, chafing and redness associated with these conditions
Pediatric tested
CHG Compatible
Can be used on denuded skin

Smith & Nephew

Secura

Antifungal Extra Thick

Made in India for:

Smith & Nephew Medical Ltd, 101 Hessle Road, Hull, HU3 2BN England

Trademark of Smith & Nephew

Certain marks Reg'd U.S. Pat & Tm. Off.

PACKAGE LABEL - PRINCIPAL DISPLAY PANEL - SECURA ANTIFUNGAL GREASELESS - TUBE(57g)

Item #59432800

NDC 69740-328-00

Antifungal Greaseless

2% Miconazole Nitrate
Cures most jock itch (tinea cruris), ringworm (tinea corporis), and athlete's foot (tinea pedis)
Relieves burning, itching, scaling, cracking, chafing and redness associated with these conditions
Pediatric tested
CHG compatible

Smith & Nephew

Secura

Antifungal Greaseless

Made in India for:

Smith & Nephew Medical Ltd, 101 Hessle Road, Hull HU3 2BN, England

Trademark of Smith & Nephew

Certain Marks Reg'd U.S. Pat & Tm. Off.